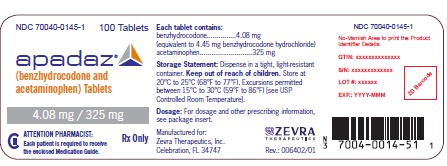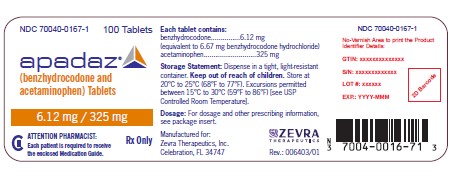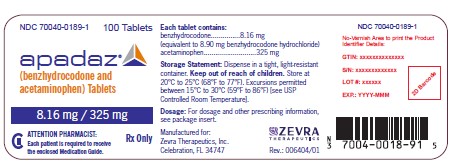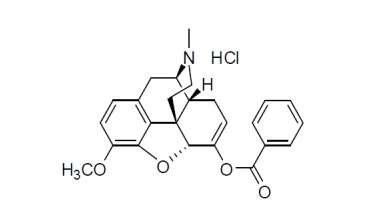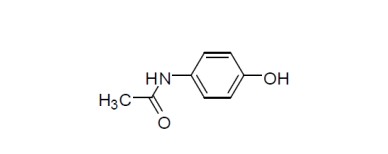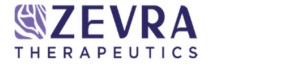 DRUG LABEL: APADAZ
NDC: 70040-0189 | Form: TABLET
Manufacturer: Zevra Therapeutics, Inc.
Category: prescription | Type: HUMAN PRESCRIPTION DRUG LABEL
Date: 20250107
DEA Schedule: CII

ACTIVE INGREDIENTS: BENZHYDROCODONE HYDROCHLORIDE 8.16 mg/1 1; ACETAMINOPHEN 325 mg/1 1
INACTIVE INGREDIENTS: CELLULOSE, MICROCRYSTALLINE; STARCH, CORN; CROSPOVIDONE; POVIDONE K30; STEARIC ACID

HIGHLIGHTS OF PRESCRIBING INFORMATION

These highlights do not include all the information needed to use APADAZ® safely and effectively. See full prescribing information for APADAZ.
APADAZ (benzhydrocodone and acetaminophen) tablets, for oral use, CII
Initial U.S. Approval: 1982

WARNING: SERIOUS AND LIFE-THREATENING RISKS FROM USE OF APADAZ

See full prescribing information for complete boxed warning.

- APADAZ exposes users to risks of addiction, abuse, and misuse, which can lead to overdose and death. Assess patient’s risk before prescribing and reassess regularly for these behaviors and conditions. (5.1)
- Serious, life-threatening, or fatal respiratory depression may occur. Monitor closely, especially upon initiation or following a dosage increase. To reduce the risk of respiratory depression, proper dosing and titration of APADAZ are essential. (5.3)
- Accidental ingestion of APADAZ, especially by children, can result in a fatal overdose of hydrocodone. (5.3)
- Concomitant use of opioids with benzodiazepines or other central nervous system (CNS) depressants, including alcohol, may result in profound sedation, respiratory depression, coma, and death. Reserve concomitant prescribing for use in patients for whom alternative treatment options are inadequate. (5.7, 7)
- If opioid use is required for an extended period of time in a pregnant woman, advise the patient of the risk of Neonatal Opioid
  Withdrawal Syndrome, which may be life-threatening if not recognized and treated. Ensure that management by neonatology
  experts will be available at delivery. (5.4)
- Healthcare providers are strongly encouraged to complete a REMS-compliant education program and to counsel patients and
  caregivers on serious risks, safe use, and the importance of reading the Medication Guide with each prescription. (5.2)
- Concomitant use with CYP3A4 inhibitors (or discontinuation of CYP3A4 inducers) can result in a fatal overdose of hydrocodone from APADAZ. (5.5, 7, 12.3)
- APADAZ contains acetaminophen. Acetaminophen has been associated with cases of acute liver failure, at times resulting in liver transplant and death. Most of the cases of liver injury are associated with the use of acetaminophen at doses that exceed 4000 milligrams per day, and often involve more than one acetaminophen-containing product. (5.6)

RECENT MAJOR CHANGES

Boxed Warning 12/2023

Indications and Usage (1) 12/2023

Dosage and Administration (2.1, 2.3, 2.5) 12/2023

Warnings and Precautions (5.8) 12/2023

1 INDICATIONS AND USAGE

APADAZ is a combination of benzhydrocodone, a prodrug of the opioid agonist hydrocodone, and acetaminophen, and is indicated for the short-term (no more than 14 days) management of acute pain severe enough to require an opioid analgesic and for which alternative treatments are inadequate. (1)

Limitations of Use(1)
Because of the risks of addiction, abuse, and misuse with opioids, which can occur at any dosage or duration, reserve APADAZ for use in patients for whom alternative treatment options [e.g., non-opioid analgesics]:

- Have not been tolerated or are not expected to be tolerated,
- Have not provided adequate analgesia or are not expected to provide adequate analgesia

APADAZ should not be used for an extended period of time unless the pain remains severe enough to require an opioid analgesic and for which alternative treatment options continue to be inadequate.

2 DOSAGE AND ADMINISTRATION

- APADAZ should be prescribed only by healthcare professionals who are knowledgeable about the use of opioids and how to mitigate the associated risks. (2.1)
- Use the lowest effective dosage for the shortest duration of time consistent with individual patient treatment goals. Reserve titration to higher doses of APADAZ for patients in whom lower doses are insufficiently effective and in whom the expected benefits of using a higher dose opioid clearly outweigh the substantial risks. (2.1, 5)
- Many acute pain conditions (e.g., the pain that occurs with a number of surgical procedures or acute musculoskeletal injuries) require no more than a few days of an opioid analgesic. Clinical guidelines on opioid prescribing for some acute pain conditions are available. (2.1)
- Initiate the dosing regimen for each patient individually, taking into account the patient’s underlying cause and severity of pain, prior analgesic treatment and response, and risk factors for addiction, abuse, and misuse. (2.1, 5.1)
- Respiratory depression can occur at any time during opioid therapy especially when initiating and following dosage increases with APADAZ. Consider this risk when selecting an initial dose and when making dose adjustments. (2.1, 5.2)
- Discuss availability of naloxone with the patient and caregiver and assess each patient’s need for access to naloxone, both when initiating and renewing treatment with APADAZ. Consider prescribing naloxone based on the patient’s risk factors for overdose (2.2, 5.1, 5.3, 5.7).
- Initiate treatment with APADAZ at 1 or 2 tablets every 4 to 6 hours as needed for pain, and at the lowest dose necessary to achieve adequate analgesia. Titrate the dose based upon the individual patient’s response to their initial dose of APADAZ. Dosage should not exceed 12 tablets in a 24- hour period. (2.5)
- See full prescribing information for conversion from hydrocodone bitartrate/acetaminophen. (2.4)
- Do not abruptly discontinue APADAZ in a physically-dependent patient because rapid discontinuation of opioid analgesics has resulted in serious withdrawal symptoms, uncontrolled pain, and suicide. (2.6, 5.16)

3 DOSAGE FORMS AND STRENGTHS

Immediate-release tablets (3):

- 4.08 mg benzhydrocodone (equivalent to 4.45 mg benzhydrocodone hydrochloride) and 325 mg acetaminophen
- 6.12 mg benzhydrocodone (equivalent to 6.67 mg benzhydrocodone hydrochloride) and 325 mg acetaminophen
- 8.16 mg benzhydrocodone (equivalent to 8.90 mg benzhydrocodone hydrochloride) and 325 mg acetaminophen

4 CONTRAINDICATIONS

- Significant respiratory depression (4)
- Acute or severe bronchial asthma in an unmonitored setting or in absence of resuscitative equipment (4)
- Known or suspected gastrointestinal obstruction, including paralytic ileus (4)
- Hypersensitivity to hydrocodone or acetaminophen (4)

5 WARNINGS AND PRECAUTIONS

- Opioid-Induced Hyperalgesia and Allodynia: Opioid-Induced Hyperalgesia (OIH) occurs when an opioid analgesic paradoxically causes an increase in pain, or an increase in sensitivity to pain. If OIH is suspected, carefully consider appropriately decreasing the dose of the current opioid analgesic, or opioid rotation. (5.8)
- Life-Threatening Respiratory Depression in Patients with Chronic Pulmonary Disease or in Elderly, Cachectic, or Debilitated Patients: Regularly evaluate closely, particularly during initiation and titration. (5.8)
- Adrenal Insufficiency: If diagnosed, treat with physiologic replacement of corticosteroids, and wean patient off of the opioid. (5.9)
- Severe Hypotension: Regularly evaluate during dosage initiation and titration. Avoid use of APADAZ in patients with circulatory shock. (5.10)
- Risks of Use in Patients with Increased Intracranial Pressure, Brain Tumors, Head Injury, or Impaired Consciousness: Monitor for sedation and respiratory depression. Avoid use of APADAZ in patients with impaired consciousness or coma. (5.12)
- Serious Skin Reactions: Discontinue APADAZ immediately at the first appearance of skin rash and if symptoms associated with allergy or hypersensitivity occur. Do not use in patients with acetaminophen allergy. (5.18)

6 ADVERSE REACTIONS

Most common adverse reactions (>5%) are nausea, somnolence, vomiting, constipation, pruritus, dizziness, and headache. (6)

To report SUSPECTED ADVERSE REACTIONS, contact Zevra Therapeutics, Inc. at 1-888-958-1253 or FDA at 1-800-FDA-1088 or www.fda.gov/medwatch.

7 DRUG INTERACTIONS

- Serotonergic Drugs: Concomitant use may result in serotonin syndrome. Discontinue APADAZ if serotonin syndrome is suspected. (7)
- Mixed Agonist/Antagonist and Partial Agonist Opioid Analgesics: Avoid use with APADAZ because they may reduce analgesic effect of APADAZ or precipitate withdrawal symptoms. (7)
- Monoamine Oxidase Inhibitors (MAOIs): Can potentiate the effects of hydrocodone. Avoid concomitant use in patients receiving MAOIs or within 14 days of stopping treatment with an MAOI. (7)

8 USE IN SPECIFIC POPULATIONS

Pregnancy: May cause fetal harm. (8.1)

FULL PRESCRIBING INFORMATION

WARNING: SERIOUS AND LIFE-THREATENING RISKS FROM USE OF APADAZ

Addiction, Abuse, and Misuse
Because the use of APADAZ exposes patients and other users to the risks of opioid addiction, abuse, and misuse, which can lead to overdose and death, assess each patient’s risk prior to prescribing and reassess all patients regularly for the development of these behaviors and conditions [see Warnings and Precautions (5.1)] .

Life-Threatening Respiratory Depression
Serious, life-threatening, or fatal respiratory depression may occur with use of APADAZ, especially during initiation or following a dosage increase. To reduce the risk of respiratory depression, proper dosing and titration of APADAZ are essential [see Warnings and Precautions (5.2)] .

Accidental Ingestion
Accidental ingestion of even one dose of APADAZ, especially by children, can result in a fatal overdose of hydrocodone [see Warnings and Precautions (5.2)] .

Risks From Concomitant Use With Benzodiazepines Or Other CNS Depressants
Concomitant use of opioids with benzodiazepines or other central nervous system (CNS) depressants, including alcohol, may result in profound sedation, respiratory depression, coma, and death. Reserve concomitant prescribing of APADAZ and benzodiazepines or other CNS depressants for use in patients for whom alternative treatment options are inadequate [see Warnings and Precautions (5.3), Drug Interactions (7)] .

Neonatal Opioid Withdrawal Syndrome (NOWS)
If opioid use is required for an extended period of time in a pregnant woman, advise the patient of the risk of NOWS, which may be life-threatening if not recognized and treated. Ensure that management by neonatology experts will be available at delivery [see Warnings and Precautions (5.4)] .

Opioid Analgesic Risk Evaluation and Mitigation Strategy (REMS)
Healthcare providers are strongly encouraged to complete a REMS-compliant education program and to counsel patients and caregivers on serious risks, safe use, and the importance of reading the Medication Guide with each prescription [see Warnings and Precautions (5.5)] .

Cytochrome P450 3A4 Interaction
The concomitant use of APADAZ with all cytochrome P450 3A4 inhibitors may result in an increase in hydrocodone plasma concentrations, which could increase or prolong adverse reactions and may cause potentially fatal respiratory depression. In addition, discontinuation of a concomitantly used cytochrome P450 3A4 inducer may result in an increase in hydrocodone plasma concentration. Regularly evaluate patients receiving APADAZ and any CYP3A4 inhibitor or inducer [see Warnings and Precautions (5.5), Drug Interactions (7), Clinical Pharmacology (12.3)] .

Hepatotoxicity
APADAZ contains acetaminophen. Acetaminophen has been associated with cases of acute liver failure, at times resulting in liver transplant and death. Most of the cases of liver injury are associated with the use of acetaminophen at doses that exceed 4000 milligrams per day, and often involve more than one acetaminophen-containing product [see Warnings and Precautions (5.6)] .

1 INDICATIONS AND USAGE

APADAZ is indicated for the short-term (no more than 14 days) management of acute pain severe enough to require an opioid analgesic and for which alternative treatments are inadequate.

Limitations of Use
Because of the risks of addiction, abuse, and misuse with opioids, which can occur at any dosage or duration [see Warnings and Precautions (5.1) ]reserve APADAZ for use in patients for whom alternative treatment options [e.g., non-opioid analgesics]:

- Have not been tolerated or are not expected to be tolerated,
- Have not provided adequate analgesia or are not expected to provide adequate analgesia.

APADAZ should not be used for an extended period of time unless the pain remains severe enough to require an opioid analgesic and for which alternative treatment options continue to be inadequate.

2 DOSAGE AND ADMINISTRATION

2.1 Important Dosage and Administration Instructions

- APADAZ should be prescribed only by healthcare professionals who are knowledgeable about the use of opioids and how to mitigate the associated risks.
- Use the lowest effective dosage for the shortest duration of time consistent with individual patient treatment goals [see Warnings and Precautions (5)] . Because the risk of overdose increases as opioid doses increase, reserve titration to higher doses of APADAZ for patients in whom lower doses are insufficiently effective and in whom the expected benefits of using a higher dose opioid clearly outweigh the substantial risks.
- The total dosage of APADAZ and any concomitant acetaminophen-containing products should not exceed 4000 mg of acetaminophen in a 24-hour period.
- Many acute pain conditions (e.g., the pain that occurs with a number of surgical procedures or acute musculoskeletal injuries) require no more than a few days of an opioid analgesic. Clinical guidelines on opioid prescribing for some acute pain conditions are available.
- There is variability in the opioid analgesic dose and duration needed to adequately manage pain due both to the cause of pain and to individual patient factors. Initiate the dosing regimen for each patient individually, taking into account the patient’s underlying cause and severity of pain, prior analgesic treatment and response, and risk factors for addiction, abuse, and misuse [see Warnings and Precautions (5.1)].
- Respiratory depression can occur at any time during opioid therapy, especially when initiating and following dosage increases with APADAZ. Consider this risk when selecting an initial dose and when making dose adjustments [ see Warnings and Precautions (5.2)] .

2.2 Patient Access to Naloxone for the Emergency Treatment of Opioid Overdose

Discuss the availability of naloxone for the emergency treatment of opioid overdose with the patient and caregiver and assess the potential need for access to naloxone, both when initiating and renewing treatment with APADAZ [see Warnings and Precautions (5.3)].

Inform patients and caregivers about the various ways to obtain naloxone as permitted by individual state naloxone dispensing and prescribing requirements or guidelines (e.g., by prescription, directly from a pharmacist, or as part of a community-based program).

Consider prescribing naloxone, based on the patient’s risk factors for overdose, such as concomitant use of CNS depressants, a history of opioid use disorder, or prior opioid overdose. The presence of risk factors for overdose should not prevent the proper management of pain in any given patient [see Warnings and Precautions (5.1, 5.2,5.3)] .

Consider prescribing naloxone if the patient has household members (including children) or other close contacts at risk for accidental ingestion or overdose.

2.3 Initial Dosage

Use of APADAZ as the First Opioid Analgesic
Initiate treatment with APADAZ at 1 to 2 tablets every 4 to 6 hours as needed for pain, at the lowest dose necessary to achieve adequate analgesia. Titrate the dose based upon the individual patient’s response to their initial dose of APADAZ. Dosage should not exceed 12 tablets in a 24-hour period.

2.4 Conversion from Other Opioids to APADAZ

There is inter-patient variability in the potency of opioid drugs and opioid formulations. Therefore, a conservative approach is advised when determining the total daily dosage of APADAZ. It is safer to underestimate a patient's 24-hour APADAZ dosage than to overestimate the 24-hour APADAZ dosage and manage an adverse reaction due to overdose.

Conversion from Hydrocodone Bitartrate/Acetaminophen to APADAZ
Patients can be converted from immediate-release hydrocodone bitartrate/acetaminophen to a dosing regimen of APADAZ as shown in Table 1.

Table 1. Conversion from Hydrocodone bitartrate/Acetaminophen to APADAZ.
Hydrocodone bitartrate doses (mg) | APADAZ equivalent (mg benzhydrocodone)
5 | 4.08
7.5 | 6.12
10 | 8.16

2.5 Titration and Maintenance of Therapy

Individually titrate APADAZ to a dose that provides adequate analgesia and minimizes adverse reactions. Continually reevaluate patients receiving APADAZ to assess the maintenance of pain control, signs and symptoms of opioid withdrawal, and other adverse reactions, as well as to reassess for the development of addiction, abuse, or misuse [see Warnings and Precautions (5.1, 5.16) ]. Frequent communication is important among the prescriber, other members of the healthcare team, the patient, and the caregiver/family during periods of changing analgesic requirements, including initial titration.

If the level of pain increases after dosage stabilization, attempt to identify the source of increased pain before increasing the APADAZ dosage. If after increasing the dosage unacceptable opioid-related adverse reactions are observed (including an increase in pain after dosage increase), consider reducing the dosage [see Warnings and Precautions (5)]. Adjust the dosage to obtain an appropriate balance between management of pain and opioid-related adverse reactions.

Total dosage of APADAZ and any concomitant acetaminophen-containing products should not exceed 4000 mg of acetaminophen in a 24-hour period.

2.6 Safe Reduction or Discontinuation of APADAZ

Do not abruptly discontinue APADAZ in patients who may be physically dependent on opioids. Rapid discontinuation of opioid analgesics in patients who are physically dependent on opioids has resulted in serious withdrawal symptoms, uncontrolled pain, and suicide. Rapid discontinuation has also been associated with attempts to find other sources of opioid analgesics, which may be confused with drug-seeking for abuse. Patients may also attempt to treat their pain or withdrawal symptoms with illicit opioids, such as heroin, and other substances.

When a decision has been made to decrease the dose or discontinue therapy in an opioid-dependent patient taking APADAZ, there are a variety of factors that should be considered, including the total daily dose of opioid (including APADAZ) the patient has been taking, the duration of treatment, the type of pain being treated, and the physical and psychological attributes of the patient. It is important to ensure ongoing care of the patient and to agree on an appropriate tapering schedule and follow-up plan so that patient and provider goals and expectations are clear and realistic. When opioid analgesics are being discontinued due to a suspected substance use disorder, evaluate and treat the patient, or refer for evaluation and treatment of the substance use disorder. Treatment should include evidence-based approaches, such as medication assisted treatment of opioid use disorder. Complex patients with comorbid pain and substance use disorders may benefit from referral to a specialist.

There are no standard opioid tapering schedules that are suitable for all patients. Good clinical practice dictates a patient-specific plan to taper the dose of the opioid gradually. For patients on APADAZ who are physically opioid-dependent, initiate the taper by a small enough increment (e.g., no greater than 10% to 25% of the total daily dose) to avoid withdrawal symptoms, and proceed with dose-lowering at an interval of every 2 to 4 weeks. Patients who have been taking opioids for briefer periods of time may tolerate a more rapid taper.

It may be necessary to provide the patient with lower dosage strengths to accomplish a successful taper. Reassess the patient frequently to manage pain and withdrawal symptoms, should they emerge. Common withdrawal symptoms include restlessness, lacrimation, rhinorrhea, yawning, perspiration, chills, myalgia, and mydriasis. Other signs and symptoms also may develop, including irritability, anxiety, backache, joint pain, weakness, abdominal cramps, insomnia, nausea, anorexia, vomiting, diarrhea, or increased blood pressure, respiratory rate, or heart rate. If withdrawal symptoms arise, it may be necessary to pause the taper for a period of time or raise the dose of the opioid analgesic to the previous dose, and then proceed with a slower taper. In addition, evaluate patients for any changes in mood, emergence of suicidal thoughts, or use of other substances.

When managing patients taking opioid analgesics, particularly those who have been treated for an extended period of time, and/or with high doses for chronic pain, ensure that a multimodal approach to pain management, including mental health support (if needed), is in place prior to initiating an opioid analgesic taper. A multimodal approach to pain management may optimize the treatment of chronic pain, as well as assist with the successful tapering of the opioid analgesic [see Warnings and Precautions (5.16), Drug Abuse and Dependence (9.3) ].

3 DOSAGE FORMS AND STRENGTHS

Immediate-release tablet.

- Capsule-shaped white tablet debossed with “KP201” on one side and “445” on the opposite side contains 4.08 mg benzhydrocodone (equivalent to 4.45 mg benzhydrocodone hydrochloride) and 325 mg acetaminophen.
- Capsule-shaped white tablet debossed with “KP201” on one side and blank on the opposite side contains 6.12 mg benzhydrocodone (equivalent to 6.67 mg benzhydrocodone hydrochloride) and 325 mg acetaminophen.
- Capsule-shaped white tablet debossed with “KP201” on one side and “890” on the opposite side contains 8.16 mg benzhydrocodone (equivalent to 8.90 mg benzhydrocodone hydrochloride) and 325 mg acetaminophen.

4 CONTRAINDICATIONS

APADAZ is contraindicated in patients with:

- Significant respiratory depression [see Warnings and Precautions (5.3)]
- Acute or severe bronchial asthma in an unmonitored setting or in the absence of resuscitative equipment [see Warnings and Precautions (5.8)]
- Known or suspected gastrointestinal obstruction, including paralytic ileus [see Warnings and Precautions (5.14)]
- Hypersensitivity to hydrocodone or acetaminophen, or any other component of this product (e.g., anaphylaxis) [see Warnings and Precautions (5.13), Adverse Reactions (6)]

5 WARNINGS AND PRECAUTIONS

5.1 Addiction, Abuse, and Misuse

APADAZ contains benzhydrocodone, a Schedule II controlled substance. As an opioid, APADAZ exposes users to the risks of addiction, abuse, and misuse [see Drug Abuse and Dependence (9) ].

Although the risk of addiction in any individual is unknown, it can occur in patients appropriately prescribed APADAZ. Addiction can occur at recommended dosages and if the drug is misused or abused.

Assess each patient’s risk for opioid addiction, abuse, or misuse prior to prescribing APADAZ, and reassess all patients receiving APADAZ for the development of these behaviors and conditions. Risks are increased in patients with a personal or family history of substance abuse (including drug or alcohol abuse or addiction) or mental illness (e.g., major depression). The potential for these risks should not, however, prevent the proper management of pain in any given patient. Patients at increased risk may be prescribed opioids such as APADAZ, but use in such patients necessitates intensive counseling about the risks and proper use of APADAZ along with frequent reevaluation for signs of addiction, abuse, and misuse. Consider prescribing naloxone for the emergency treatment of opioid overdose [see Dosage and Administration (2.2), Warnings and Precautions (5.3)] .

Opioids are sought for nonmedical use and are subject to diversion from legitimate prescribed use. Consider these risks when prescribing or dispensing APADAZ. Strategies to reduce these risks include prescribing the drug in the smallest appropriate quantity and advising the patient on careful storage of the drug during the course of treatment and the proper disposal of unused drug. Contact local state professional licensing board or state-controlled substances authority for information on how to prevent and detect abuse or diversion of this product.

5.2 Life-Threatening Respiratory Depression

Serious, life-threatening, or fatal respiratory depression has been reported with the use of opioids, even when used as recommended. Respiratory depression, if not immediately recognized and treated, may lead to respiratory arrest and death. Management of respiratory depression may include close observation, supportive measures, and use of opioid antagonists, depending on the patient’s clinical status [see Overdosage (10)] . Carbon dioxide (CO2) retention from opioid-induced respiratory depression can exacerbate the sedating effects of opioids.

While serious, life-threatening, or fatal respiratory depression can occur at any time during the use of APADAZ, the risk is greatest during the initiation of therapy or following a dosage increase of APADAZ.

To reduce the risk of respiratory depression, proper dosing and titration of APADAZ are essential [see Dosage and Administration (2)] . Overestimating the APADAZ dosage when converting patients from another opioid product can result in a fatal overdose with the first dose.

Accidental ingestion of even one dose of APADAZ, especially by children, can result in respiratory depression and death due to an overdose of hydrocodone.

Educate patients and caregivers on how to recognize respiratory depression and emphasize the importance of calling 911 or getting emergency medical help right away in the event of a known or suspected overdose.

Opioids can cause sleep-related breathing disorders including central sleep apnea (CSA) and sleep-related hypoxemia. Opioid use increases the risk of CSA in a dose-dependent fashion. In patients who present with CSA, consider decreasing the opioid dosage using best practices for opioid taper [see Dosage and Administration (2.6)] .

Patient Access to Naloxone for the Emergency Treatment of Opioid Overdose

Discuss the availability of naloxone for the emergency treatment of opioid overdose with the patient and caregiver and assess the potential need for access to naloxone, both when initiating and renewing treatment with APADAZ. Inform patients and caregivers about the various ways to obtain naloxone as permitted by individual state naloxone dispensing and prescribing requirements or guidelines (e.g., by prescription, directly from a pharmacist, or as part of a community-based program). Educate patients and caregivers on how to recognize respiratory depression and emphasize the importance of calling 911 or getting emergency medical help, even if naloxone is administered.

Consider prescribing naloxone, based on the patient’s risk factors for overdose, such as concomitant use of CNS depressants, a history of opioid use disorder, or prior opioid overdose. The presence of risk factors for overdose should not prevent the proper management of pain in any given patient. Also consider prescribing naloxone if the patient has household members (including children) or other close contacts at risk for accidental ingestion or overdose. If naloxone is prescribed, educate patients and caregivers on how to treat with naloxone [see Warnings and Precautions (5.1, 5.7), Overdosage (10)].

5.3 Risks from Concomitant Use with Benzodiazepines or Other CNS Depressants

Profound sedation, respiratory depression, coma, and death may result from the concomitant use of APADAZ with benzodiazepines and/or other CNS depressants, including alcohol (e.g., non-benzodiazepine sedatives/hypnotics, anxiolytics, tranquilizers, muscle relaxants, general anesthetics, antipsychotics, other opioids). Because of these risks, reserve concomitant prescribing of these drugs for use in patients for whom alternative treatment options are inadequate.

Observational studies have demonstrated that concomitant use of opioid analgesics and benzodiazepines increases the risk of drug-related mortality compared to use of opioid analgesics alone. Because of similar pharmacological properties, it is reasonable to expect similar risk with the concomitant use of other CNS depressant drugs with opioid analgesics [see Drug Interactions (7)].

If the decision is made to prescribe a benzodiazepine or other CNS depressant concomitantly with an opioid analgesic, prescribe the lowest effective dosages and minimum durations of concomitant use. In patients already receiving an opioid analgesic, prescribe a lower initial dose of the benzodiazepine or other CNS depressant than indicated in the absence of an opioid, and titrate based on clinical response. If an opioid analgesic is initiated in a patient already taking a benzodiazepine or other CNS depressant, prescribe a lower initial dose of the opioid analgesic, and titrate based on clinical response. Inform patients and caregivers of this potential interaction and educate them on the signs and symptoms of respiratory depression (including sedation).

If concomitant use is warranted, consider prescribing naloxone for the emergency treatment of opioid overdose [see Dosage and Administration (2.2), Warnings and Precautions (5.3), Overdosage (10)] .

Advise both patients and caregivers about the risks of respiratory depression and sedation when APADAZ is used with benzodiazepines or other CNS depressants (including alcohol and illicit drugs). Advise patients not to drive or operate heavy machinery until the effects of concomitant use of the benzodiazepine or other CNS depressant have been determined. Screen patients for risk of substance use disorders, including opioid abuse and misuse, and warn them of the risk for overdose and death associated with the use of additional CNS depressants including alcohol and illicit drugs [see Drug Interactions (7)].

5.4 Neonatal Opioid Withdrawal Syndrome

Use of APADAZ for an extended period of time during pregnancy can result in withdrawal in the neonate. Neonatal opioid withdrawal syndrome, unlike opioid withdrawal syndrome in adults, may be life-threatening if not recognized and treated, and requires management according to protocols developed by neonatology experts. Observe newborns for signs of neonatal opioid withdrawal syndrome and manage accordingly. Advise pregnant women using opioids for an extended period of time of the risk of neonatal opioid withdrawal syndrome and ensure that appropriate treatment will be available [see Use in Specific Populations (8.1)].

5.5 Opioid Analgesic Risk Evaluation and Mitigation Strategy (REMS)

To ensure that the benefits of opioid analgesics outweigh the risks of addiction, abuse, and misuse, the Food and Drug Administration (FDA) has required a Risk Evaluation and Mitigation Strategy (REMS) for these products. Under the requirements of the REMS, drug companies with approved opioid analgesic products must make REMS-compliant education programs available to healthcare providers. Healthcare providers are strongly encouraged to do all of the following:

- Complete a REMS-compliant education programoffered by an accredited provider of continuing education (CE) or another education program that includes all the elements of the FDA Education Blueprint for Health Care Providers Involved in the Management or Support of Patients with Pain.
- Discuss the safe use, serious risks, and proper storage and disposal of opioid analgesics with patients and/or their caregivers every time these medicines are prescribed. The Patient Counseling Guide (PCG) can be obtained at this link: www.fda.gov/OpioidAnalgesicREMSPCG
- Emphasize to patients and their caregivers the importance of reading the Medication Guide that they will receive from their pharmacist every time an opioid analgesic is dispensed to them.
- Consider using other tools to improve patient, household, and community safety, such as patient-prescriber agreements that reinforce patient-prescriber responsibilities.

To obtain further information on the opioid analgesic REMS and for a list of accredited REMS CME/CE, call 1-800-503-0784, or log on to www.opioidanalgesicrems.com. The FDA Blueprint can be found at www.fda.gov/OpioidAnalgesicREMSBlueprint.

5.6 Risks of Concomitant Use or Discontinuation of Cytochrome P450 CYP3A4 Inhibitors and Inducers

Concomitant use of APADAZ with a CYP3A4 inhibitor, such as macrolide antibiotics (e.g., erythromycin), azole-antifungal agents (e.g., ketoconazole), and protease inhibitors (e.g., ritonavir), may increase plasma concentrations of hydrocodone and prolong opioid adverse reactions, which may cause potentially fatal respiratory depression [see Warnings and Precautions (5.3)] , particularly when an inhibitor is added after a stable dose of APADAZ is achieved. Similarly, discontinuation of a CYP3A4 inducer, such as rifampin, carbamazepine, and phenytoin, in APADAZ-treated patients may increase hydrocodone plasma concentrations and prolong opioid adverse reactions. When using APADAZ with CYP3A4 inhibitors or discontinuing CYP3A4 inducers in APADAZ-treated patients, evaluate patients closely at frequent intervals and consider dosage reduction of APADAZ until stable drug effects are achieved [see Drug Interactions (7)] .

Concomitant use of APADAZ with CYP3A4 inducers or discontinuation of an CYP3A4 inhibitor could decrease hydrocodone plasma concentrations, decrease opioid efficacy or, possibly, lead to a withdrawal syndrome in a patient who had developed physical dependence to hydrocodone. When using APADAZ with CYP3A4 inducers or discontinuing CYP3A4 inhibitors, evaluate patients closely at frequent intervals and consider increasing the opioid dosage if needed to maintain adequate analgesia or if symptoms of opioid withdrawal occur [see Drug Interactions (7)] .

5.7 Acetaminophen Hepatotoxicity

APADAZ contains acetaminophen. Acetaminophen has been associated with cases of acute liver failure, at times resulting in liver transplant and death. Most of the cases of liver injury are associated with the use of acetaminophen at doses that exceed 4000 milligrams per day, and often involve more than one acetaminophen-containing product [see Overdosage (10)] . The excessive intake of acetaminophen may be intentional to cause self-harm or unintentional as patients attempt to obtain more pain relief or unknowingly take other acetaminophen-containing products.

The risk of acute liver failure is higher in individuals with underlying liver disease and in individuals who ingest alcohol while taking acetaminophen.

Instruct patients to look for “acetaminophen” or “APAP” on package labels and not to use more than one product that contains acetaminophen. Instruct patients to seek medical attention immediately upon ingestion of more than 4000 milligrams of acetaminophen per day, even if they feel well.

5.8 Opioid-Induced Hyperalgesia and Allodynia

Opioid-Induced Hyperalgesia (OIH) occurs when an opioid analgesic paradoxically causes an increase in pain, or an increase in sensitivity to pain. This condition differs from tolerance, which is the need for increasing doses of opioids to maintain a defined effect [see Dependence (9.3)] . Symptoms of OIH include (but may not be limited to) increased levels of pain upon opioid dosage increase, decreased levels of pain upon opioid dosage decrease, or pain from ordinarily non-painful stimuli (allodynia). These symptoms may suggest OIH only if there is no evidence of underlying disease progression, opioid tolerance, opioid withdrawal, or addictive behavior.

Cases of OIH have been reported, both with short-term and longer-term use of opioid analgesics. Though the mechanism of OIH is not fully understood, multiple biochemical pathways have been implicated. Medical literature suggests a strong biologic plausibility between opioid analgesics and OIH and allodynia. If a patient is suspected to be experiencing OIH, carefully consider appropriately decreasing the dose of the current opioid analgesic or opioid rotation (safely switching the patient to a different opioid moiety) [see Dosage and Administration (2.6), Warnings and Precautions (5.16)] .

5.9 Life-Threatening Respiratory Depression in Patients with Chronic Pulmonary Disease or in Elderly, Cachectic, or Debilitated Patients

The use of APADAZ in patients with acute or severe bronchial asthma in an unmonitored setting or in the absence of resuscitative equipment is contraindicated.

Patients with Chronic Pulmonary Disease:APADAZ-treated patients with significant chronic obstructive pulmonary disease or cor pulmonale, and those with a substantially decreased respiratory reserve, hypoxia, hypercapnia, or pre-existing respiratory depression are at increased risk of decreased respiratory drive including apnea, even at recommended dosages of APADAZ [see Warnings and Precautions (5.3)] .

Elderly, Cachectic, or Debilitated Patients:Life-threatening respiratory depression is more likely to occur in elderly, cachectic, or debilitated patients because they may have altered pharmacokinetics or altered clearance compared to younger, healthier patients [see Warnings and Precautions (5.3)] .

Regularly evaluate such patients, particularly when initiating and titrating APADAZ and when APADAZ is given concomitantly with other drugs that depress respiration [see Warnings and Precautions (5.3)] . Alternatively, consider the use of non-opioid analgesics in these patients.

5.10 Adrenal Insufficiency

Cases of adrenal insufficiency have been reported with opioid use, more often following greater than one month of use. Presentation of adrenal insufficiency may include non-specific symptoms and signs including nausea, vomiting, anorexia, fatigue, weakness, dizziness, and low blood pressure. If adrenal insufficiency is suspected, confirm the diagnosis with diagnostic testing as soon as possible. If adrenal insufficiency is diagnosed, treat with physiologic replacement doses of corticosteroids. Wean the patient off of the opioid to allow adrenal function to recover and continue corticosteroid treatment until adrenal function recovers. Other opioids may be tried as some cases reported use of a different opioid without recurrence of adrenal insufficiency. The information available does not identify any particular opioids as being more likely to be associated with adrenal insufficiency.

5.11 Severe Hypotension

APADAZ may cause severe hypotension including orthostatic hypotension and syncope in ambulatory patients. There is increased risk in patients whose ability to maintain blood pressure has already been compromised by a reduced blood volume or concurrent administration of certain CNS depressant drugs (e.g., phenothiazines or general anesthetics) [see Drug Interactions (7)] . Regularly evaluate these patients for signs of hypotension after initiating or titrating the dosage of APADAZ.

In patients with circulatory shock, APADAZ may cause vasodilation that can further reduce cardiac output and blood pressure. Avoid the use of APADAZ in patients with circulatory shock.

5.12 Risks of Use in Patients with Increased Intracranial Pressure, Brain Tumors, Head Injury, or Impaired Consciousness

In patients who may be susceptible to the intracranial effects of CO2retention (e.g., those with evidence of increased intracranial pressure or brain tumors), APADAZ may reduce respiratory drive, and the resultant CO2retention can further increase intracranial pressure. Monitor such patients for signs of sedation and respiratory depression, particularly when initiating therapy with APADAZ.

Opioids may also obscure the clinical course in a patient with a head injury. Avoid the use of APADAZ in patients with impaired consciousness or coma.

5.13 Risks of Use in Patients with Gastrointestinal Conditions

APADAZ is contraindicated in patients with known or suspected gastrointestinal obstruction, including paralytic ileus.

The hydrocodone from APADAZ may cause spasm of the sphincter of Oddi. Opioids may cause increases in serum amylase. Regularly evaluate patients with biliary tract disease, including acute pancreatitis for worsening symptoms.

5.14 Hypersensitivity/Anaphylaxis

There have been post-marketing reports of hypersensitivity and anaphylaxis associated with use of acetaminophen. Clinical signs included swelling of the face, mouth, and throat, respiratory distress, urticaria, rash, pruritus, and vomiting. There were infrequent reports of life-threatening anaphylaxis requiring emergency medical attention. Instruct patients to discontinue APADAZ tablets immediately and seek medical care if they experience these symptoms. Do not prescribe APADAZ tablets for patients with acetaminophen allergy.

5.15 Increased Risk of Seizures in Patients with Seizure Disorders

The hydrocodone from APADAZ may increase the frequency of seizures in patients with seizure disorders and may increase the risk of seizures occurring in other clinical settings associated with seizures. Regularly evaluate patients with a history of seizure disorders for worsened seizure control during APADAZ therapy.

5.16 Withdrawal

Do not abruptly discontinue APADAZ in a patient physically dependent on opioids. When discontinuing APADAZ in a physically dependent patient, gradually taper the dosage. Rapid tapering of APADAZ in a patient physically dependent on opioids may lead to a withdrawal syndrome and return of pain [see Dosage and Administration (2.6), Drug Abuse and Dependence (9.3)].

Additionally, avoid the use of mixed agonist/antagonist (e.g., pentazocine, nalbuphine, and butorphanol) or partial agonist (e.g., buprenorphine) analgesics in patients who are receiving a full opioid agonist analgesic, including APADAZ. In these patients, mixed agonist/antagonist and partial agonist analgesics may reduce the analgesic effect and/or may precipitate withdrawal symptoms. [see Drug Interactions (7)].

5.17 Risks of Driving and Operating Machinery

APADAZ may impair the mental or physical abilities needed to perform potentially hazardous activities such as driving a car or operating machinery. Warn patients not to drive or operate dangerous machinery unless they are tolerant to the effects of APADAZ and know how they will react to the medication.

5.18 Serious Skin Reactions

Rarely, acetaminophen may cause serious skin reactions such as acute generalized exanthematous pustulosis (AGEP), Stevens-Johnson Syndrome (SJS), and toxic epidermal necrolysis (TEN), which can be fatal. Inform patients about the signs of serious skin reactions and discontinue use at the first appearance of skin rash or any other sign of hypersensitivity.

6 ADVERSE REACTIONS

The following serious adverse reactions are described, or described in greater detail, in other sections:

- Addiction, Abuse, and Misuse [see Warnings and Precautions (5.1)]
- Life-Threatening Respiratory Depression [see Warnings and Precautions (5.2)]
- Interactions with Benzodiazepines and other CNS Depressants [see Warnings and Precautions (5.3)]
- Neonatal Opioid Withdrawal Syndrome [see Warnings and Precautions (5.4)]
- Hepatotoxicity [see Warnings and Precautions (5.7)]
- Opioid-Induced Hyperalgesia and Allodynia [see Warnings and Precautions (5.9)]
- Adrenal Insufficiency [see Warnings and Precautions (5.10)]
- Severe Hypotension [see Warnings and Precautions (5.11)]
- Serious Skin Reactions [see Warnings and Precautions (5.18)]
- Gastrointestinal Adverse Reactions [see Warnings and Precautions (5.13)]
- Anaphylaxis and Other Hypersensitivity Reactions [see Warnings and Precautions (5.14)]
- Seizures [see Warnings and Precautions (5.15)]
- Withdrawal [see Warnings and Precautions (5.16)]

6.1 Clinical Trials Experience

Because clinical trials are conducted under widely varying conditions, adverse reaction rates observed in clinical trials of a drug cannot be directly compared to rates in the clinical trials of another drug and may not reflect the rates observed in practice.

The safety of APADAZ was evaluated in six Phase 1 studies in which a total of 200 healthy adult subjects receive at least one oral dose of APADAZ. The most common AEs (>5%) reported across these studies were: nausea (21.5%), somnolence (18.5%), vomiting (13.0%), constipation (12.0%), pruritus (11.5%), dizziness (7.5%), and headache (6.0%).

The following adverse reactions occurred with an incidence of 1% to 5% in single-dose or repeated-dose clinical trials of APADAZ.

Gastrointestinal disorder:abdominal distension, abdominal pain, flatulence

General disorders and administration site conditions:asthenia

Nervous system disorders:presyncope, tremor

Respiratory, thoracic and mediastinal disorders:dyspnea

Vascular disorders:hot flush, hypotension

Adverse reactions occurring at less than 1%: the following lists clinically relevant adverse reactions that occurred with an incidence of less than 1% in APADAZ clinical trials.

Eye disorders:eye pruritus

Gastrointestinal disorders:diarrhea, gastroesophageal reflux disease, haematemesis

General disorders and administration site conditions:chest discomfort

Infections and infestations:rhinitis

Nervous system disorders:hypoesthesia, syncope

Psychiatric disorders:agitation, euphoric mood, nightmare

6.2 Postmarketing Experience

The following adverse reactions have been identified during post-approval use of hydrocodone. Because these reactions are reported voluntarily from a population of uncertain size, it is not always possible to reliably estimate their frequency or establish a causal relationship to drug exposure.

Serotonin syndrome: Cases of serotonin syndrome, a potentially life-threatening condition, have been reported during concomitant use of opioids with serotonergic drugs.

Adrenal insufficiency: Cases of adrenal insufficiency have been reported with opioid use, more often following greater than one month of use.

Anaphylaxis: Anaphylaxis has been reported with ingredients contained in APADAZ.

Androgen deficiency: Cases of androgen deficiency have occurred with use of opioids for an extended period of time [see Clinical Pharmacology (12.2)].

Hyperalgesia and Allodynia: Cases of hyperalgesia and allodynia have been reported with opioid therapy of any duration [see Warnings and Precautions (5.8)]

Hypoglycemia: Cases of hypoglycemia have been reported in patients taking opioids. Most reports were in patients with at least one predisposing risk factor (e.g., diabetes).

7 DRUG INTERACTIONS

Table 2. Clinically Significant Drug Interactions with APADAZ.
CYP3A4 and 2D6 Inhibitors
Clinical Impact: | The concomitant use of APADAZ and CYP3A4 inhibitors can increase the plasma concentration of hydrocodone, resulting in increased or prolonged opioid effects. These effects could be more pronounced with concomitant use of APADAZ and CYP2D6 and CYP3A4 inhibitors, particularly when an inhibitor is added after a stable dose of APADAZ is achieved [see Warnings and Precautions (5.5)] .; After stopping a CYP3A4 inhibitor, as the effects of the inhibitor decline, the hydrocodone plasma concentration will decrease [see Clinical Pharmacology (12.3)] , resulting in decreased opioid efficacy or a withdrawal syndrome in patients who had developed physical dependence to hydrocodone.
Intervention: | If concomitant use is necessary, consider dosage reduction of APADAZ until stable drug effects are achieved. Evaluate patients at frequent intervals for respiratory depression and sedation at.; If a CYP3A4 inhibitor is discontinued, consider increasing the APADAZ dosage until stable drug effects are achieved. Assess for signs of opioid withdrawal.
Examples: | Macrolide antibiotics (e.g., erythromycin), azole-antifungal agents (e.g., ketoconazole), protease inhibitors (e.g., ritonavir) etc.
CYP3A4 Inducers
Clinical Impact: | The concomitant use of APADAZ and CYP3A4 inducers can decrease the plasma concentration of hydrocodone [see Clinical Pharmacology (12.3)] , resulting in decreased efficacy or onset of a withdrawal syndrome in patients who have developed physical dependence to hydrocodone [see Warnings and Precautions (5.16)] .; After stopping a CYP3A4 inducer, as the effects of the inducer decline, the hydrocodone plasma concentration will increase [see Clinical Pharmacology (12.3)] , which could increase or prolong both the therapeutic effects and adverse reactions, and may cause serious respiratory depression.
Intervention: | If concomitant use is necessary, consider increasing the APADAZ dosage until stable drug effects are achieved [see Dosage and Administration (2)] . Assess for signs of opioid withdrawal. If a CYP3A4 inducer is discontinued, consider APADAZ dosage reduction and evaluate patients at frequent intervals for signs of respiratory depression and sedation.
Examples: | Rifampin, carbamazepine, phenytoin etc.
Benzodiazepines and Other Central Nervous System (CNS) Depressants
Clinical Impact: | Due to additive pharmacologic effect, the concomitant use of benzodiazepines or other CNS depressants, including alcohol, increases the risk of hypotension, respiratory depression, profound sedation, coma, and death.
Intervention: | Reserve concomitant prescribing of these drugs for use in patients for whom alternative treatment options are inadequate. Limit dosages and durations to the minimum required. Inform patients and caregivers of this potential interaction and educate them on the signs and symptoms of respiratory depression (including sedation). If concomitant use is warranted, consider prescribing naloxone for the emergency treatment of opioid overdose [see Dosage and Administration (2.2), Warnings and Precautions (5.1, 5.3, 5.7)] .
Examples: | Benzodiazepines and other sedatives/hypnotics, anxiolytics, tranquilizers, muscle relaxants, general anesthetics, antipsychotics, other opioids, alcohol.
Serotonergic Drugs
Clinical Impact: | The concomitant use of opioids with other drugs that affect the serotonergic neurotransmitter system has resulted in serotonin syndrome.
Intervention: | If concomitant use is warranted, frequently evaluate the patient, particularly during treatment initiation and dose adjustment. Discontinue APADAZ if serotonin syndrome is suspected.
Examples: | Selective serotonin reuptake inhibitors (SSRIs), serotonin and norepinephrine reuptake inhibitors (SNRIs), tricyclic antidepressants (TCAs), triptans, 5-HT3 receptor antagonists, drugs that affect the serotonin neurotransmitter system (e.g., mirtazapine, trazodone, tramadol), certain muscle relaxants (i.e. cyclobenzaprine, metaxalone), monoamine oxidase (MAO) inhibitors (those intended to treat psychiatric disorders and also others, such as linezolid and intravenous methylene blue).
Monoamine Oxidase Inhibitors (MAOIs)
Clinical Impact: | MAOI interactions with opioids may manifest as serotonin syndrome or opioid toxicity (e.g., respiratory depression, coma) [see Warnings and Precautions (5.3)] .; If urgent use of an opioid is necessary, use test doses and frequent titration of small doses to treat pain while closely monitoring blood pressure and signs and symptoms of CNS and respiratory depression.
Intervention: | The use of APADAZ is not recommended for patients taking MAOIs or within 14 days of stopping such treatment.
Examples: | phenelzine, tranylcypromine, linezolid
Mixed Agonist/Antagonist and Partial Agonist Opioid Analgesics
Clinical Impact: | May reduce the analgesic effect of APADAZ and/or precipitate withdrawal symptoms.
Intervention: | Avoid concomitant use.
Examples: | butorphanol, nalbuphine, pentazocine, buprenorphine
Muscle Relaxants
Clinical Impact: | Hydrocodone may enhance the neuromuscular blocking action of skeletal muscle relaxants and produce an increased degree of respiratory depression.
Intervention: | Because respiratory depression may be greater than otherwise expected, decrease the dosage of APADAZ and/or the muscle relaxant as necessary. Due to the risk of respiratory depression with concomitant use of skeletal muscle relaxants and opioids, consider prescribing naloxone for the emergency treatment of opioid overdose [see Dosage and Administration (2.2), Warnings and Precautions (5.3, 5.7)] .
Examples: | Cyclobenzaprine, metaxalone
Diuretics
Clinical Impact: | Opioids can reduce the efficacy of diuretics by inducing the release of antidiuretic hormone.
Intervention: | Evaluate patients for signs of diminished diuresis and/or effects on blood pressure and increase the dosage of the diuretic as needed.
Anticholinergic Drugs
Clinical Impact: | The concomitant use of anticholinergic drugs may increase risk of urinary retention and/or severe constipation, which may lead to paralytic ileus.
Intervention: | Evaluate patients for signs of urinary retention or reduced gastric motility when APADAZ is used concomitantly with anticholinergic drugs.

8 USE IN SPECIFIC POPULATIONS

8.1 Pregnancy

Risk Summary
Use of opioid analgesics for an extended period of time during pregnancy may cause neonatal opioid withdrawal syndrome [see Warnings and Precautions (5.4)] . There are no available human data on hydrocodone or APADAZ use during pregnancy to inform any drug associated risks. However, neonatal opioid withdrawal and other adverse reactions during pregnancy and labor can occur with use of APADAZ [see Clinical Considerations] .

Published studies with oral acetaminophen use during pregnancy have not reported an association with major congenital malformations. No reproductive or developmental toxicology studies in animals have been conducted with benzhydrocodone or the combination of benzhydrocodone and acetaminophen. Reproductive and developmental studies in rats and mice from the published literature identified adverse events at clinically relevant doses with acetaminophen. Treatment of pregnant rats with doses of acetaminophen approximately equal to the maximum human daily dose (MHDD) showed evidence of fetotoxicity and increases in bone variations in the fetuses. In another study, necrosis was observed in the liver and kidney of both pregnant rats and fetuses at doses approximately equal to the MHDD. In mice and rats treated with acetaminophen at doses within the clinical dosing range, cumulative adverse effects on reproductive capacity were reported. In mice, a reduction in number of litters of the parental mating pair was observed as well as retarded growth, abnormal sperm in their offspring, and reduced birth weight in the next generation. In rats, female fertility was decreased following in utero exposure to acetaminophen [see Data] .

The background risk of major birth defects and miscarriage for the indicated population is unknown. All pregnancies have a background risk of birth defect, loss, or other adverse outcomes. In the U.S. general population, the estimated background risk of major birth defects and miscarriage in clinically recognized pregnancies is 2 to 4% and 15 to 20%, respectively.

Clinical Considerations
Fetal/Neonatal Adverse Reactions
Use of opioid analgesics for an extended period of time during pregnancy for medical or nonmedical purposes can result in physical dependence in the neonate and neonatal opioid withdrawal syndrome shortly after birth.

Neonatal opioid withdrawal syndrome presents as irritability, hyperactivity and abnormal sleep pattern, high pitched cry, tremor, vomiting, diarrhea and failure to gain weight. The onset, duration, and severity of neonatal opioid withdrawal syndrome vary based on the specific opioid used, duration of use, timing and amount of last maternal use, and rate of elimination of the drug by the newborn. Observe newborns for symptoms of neonatal opioid withdrawal syndrome and manage accordingly [see Warnings and Precautions (5.4)] .

Labor or Delivery
Opioids cross the placenta and may produce respiratory depression and psycho-physiologic effects in neonates. An opioid antagonist, such as naloxone, must be available for reversal of opioid-induced respiratory depression in the neonate. APADAZ is not recommended for use in pregnant women during or immediately prior to labor, when other analgesic techniques are more appropriate. Opioid analgesics, including APADAZ, can prolong labor through actions which temporarily reduce the strength, duration, and frequency of uterine contractions. However, this effect is not consistent and may be offset by an increased rate of cervical dilation, which tends to shorten labor. Monitor neonates exposed to opioid analgesics during labor for signs of excess sedation and respiratory depression.

Data
Human Data

Acetaminophen:
Published data from a large population-based prospective cohort study and a population-based, case-control study do not clearly report an association with oral acetaminophen and major birth defects, miscarriage, or adverse maternal or fetal outcomes when acetaminophen is used during pregnancy. However, these studies cannot definitely establish the absence of any risk because of methodological limitations including recall bias.

Animal Data
No reproductive or developmental toxicology studies were conducted with benzhydrocodone or the combination of benzhydrocodone and acetaminophen. The following data are based on findings from studies performed with acetaminophen alone.

Studies in pregnant rats that received oral acetaminophen during organogenesis at doses up to 0.88 the maximum human daily dose (MHDD) of 3.9 grams/day based on a body surface area comparison showed evidence of fetotoxicity (reduced fetal weight and length) and a dose-related increase in bone variations (reduced ossification and rudimentary rib changes). Offspring had no evidence of external, visceral, or skeletal malformations. When pregnant rats received oral acetaminophen throughout gestation at doses of 1.2 times the MHDD (based on a body surface area comparison), areas of necrosis occurred in both the liver and kidney of pregnant rats and fetuses. These effects did not occur in
animals that received oral acetaminophen at doses 0.3 times the MHDD, based on a body surface area comparison. In a continuous breeding study, pregnant mice received 0.25, 0.5, or 1.0% acetaminophen via the diet (357, 715, or 1430 mg/kg/day). These doses are approximately 0.45, 0.89, and 1.78 times the MHDD, respectively, based on a body surface area comparison. A dose-related reduction in body weights of fourth and fifth litter offspring of the treated mating pair occurred during lactation and post-weaning at all doses. Animals in the high dose group had a reduced number of litters per mating pair, male offspring with an increased percentage of abnormal sperm, and reduced birth weights in the next generation pups.

8.2 Lactation

Risk Summary
Hydrocodone is present in human milk. A published lactation study reports variable concentrations of hydrocodone and hydromorphone (an active metabolite) in breast milk with administration of hydrocodone to nursing mothers in the early post-partum period. This lactation study did not assess breastfed infants for potential adverse drug reactions. There is potential for sedation and respiratory depression resulting from infant exposure to hydrocodone and its metabolites in breast milk.

Acetaminophen is present in human milk in small quantities after oral administration. Based on data from more than 15 nursing mothers, the calculated infant daily dose of acetaminophen is approximately 1 to 2% of the maternal dose. There is one well-documented report of a rash in a breastfed infant that resolved when the mother stopped acetaminophen use and recurred when she resumed acetaminophen use.

The developmental and health benefits of breastfeeding should be considered along with the mother’s clinical need for APADAZ and any potential adverse effects on the breastfed child from APADAZ or from the underlying maternal condition.

Clinical Considerations
Monitor infants exposed to APADAZ through breast milk for excess sedation and respiratory depression. Withdrawal symptoms can occur in breastfed infants when maternal administration of an opioid analgesic is stopped, or when breastfeeding is stopped.

8.3 Females and Males of Reproductive Potential

Infertility
Use of opioids for an extended period of time may cause reduced fertility in females and males of reproductive potential. It is not known whether these effects on fertility are reversible [see Adverse Reactions (6.2), Clinical Pharmacology (12.2)] .

Published animal studies report that oral acetaminophen treatment of male animals at doses that are 1.2 times the MHDD and greater (based on a body surface area comparison) result in decreased testicular weights, reduced spermatogenesis, reduced fertility, and reduced implantation sites in females given the same doses. Additional published animal studies indicate that acetaminophen exposure in utero adversely impacts reproductive capacity of both male and female offspring at clinically relevant exposures [see Nonclinical Toxicology (13.1)] .

8.4 Pediatric Use

Safety and effectiveness in pediatric patients below the age of 18 years have not been established.

8.5 Geriatric Use

Elderly patients (aged 65 years or older) may have increased sensitivity to hydrocodone. In general, use caution when selecting a dosage for an elderly patient, usually starting at the low end of the dosing range, reflecting the greater frequency of decreased hepatic, renal, or cardiac function and of concomitant disease or other drug therapy.

Respiratory depression is the chief risk for elderly patients treated with opioids and has occurred after large initial doses were administered to patients who were not opioid-tolerant or when opioids were co-administered with other agents that depress respiration. Titrate the dosage of APADAZ slowly in geriatric patients and frequently reevaluate the patient for signs of respiratory depression [see Warnings and Precautions (5.9)] .

Hydrocodone and acetaminophen are known to be substantially excreted by the kidney, and the risk of adverse reactions to this drug may be greater in patients with impaired renal function. Because elderly patients are more likely to have decreased renal function, care should be taken in dose selection, and it may be useful to regularly evaluate renal function.

8.6 Hepatic Impairment

The effect of hepatic impairment on the pharmacokinetics of APADAZ has not been determined. Patients with hepatic impairment may have higher plasma concentrations than those with normal function. Use a low initial dose of APADAZ in patients with hepatic impairment or active liver disease and regularly evaluate for adverse events such as respiratory depression and hepatotoxicity [see Warnings and Precautions (5.3, 5.6)] .

8.7 Renal Impairment

The effect of renal impairment on the pharmacokinetics of APADAZ has not been determined. Patients with renal impairment may have higher plasma concentrations than those with normal function. Use a low initial dose of APADAZ in patients with renal impairment and regularly evaluate for adverse events such as respiratory depression.

9 DRUG ABUSE AND DEPENDENCE

9.1 Controlled Substance

APADAZ contains benzhydrocodone, a Schedule II controlled substance.

9.2 Abuse

APADAZ contains benzhydrocodone, a substance with a high potential for misuse and abuse, which can lead to the development of substance use disorder, including addiction [see Warnings and Precautions (5.1)] .

Misuse is the intentional use, for therapeutic purposes, of a drug by an individual in a way other than prescribed by a healthcare provider or for whom it was not prescribed.

Abuse is the intentional, non-therapeutic use of a drug, even once, for its desirable psychological or physiological effects.

Drug addiction is a cluster of behavioral, cognitive, and physiological phenomena that may include a strong desire to take the drug, difficulties in controlling its use (e.g., continuing drug use despite harmful consequences, giving a higher priority to drug use than other activities and obligations), and possible tolerance or physical dependence.

Misuse and abuse of APADAZ increases risk of overdose, which may lead to central nervous system and respiratory depression, hypotension, seizures, and death. The risk is increased with concurrent abuse of APADAZ with alcohol and/or other CNS depressants. Abuse of and addiction to opioids in some individuals may not be accompanied by concurrent tolerance and symptoms of physical dependence. In addition, abuse of opioids can occur in the absence of addiction.

All patients treated with opioids require careful and frequent re-evaluation for signs of misuse, abuse, and addiction, because use of opioid analgesic products carries the risk of addiction even under appropriate medical use. Patients at high risk of APADAZ abuse include those with a history of prolonged use of any opioid, including products containing benzhydrocodone, those with a history of drug or alcohol abuse, or those who use APADAZ in combination with other abused drugs.

“Drug-seeking” behavior is very common in persons with substance use disorders. Drug-seeking tactics include emergency calls or visits near the end of office hours, refusal to undergo appropriate examination, testing, or referral, repeated “loss” of prescriptions, tampering with prescriptions, and reluctance to provide prior medical records or contact information for other treating healthcare provider(s). “Doctor shopping” (visiting multiple prescribers to obtain additional prescriptions) is common among people who abuse drugs and people with substance use disorder. Preoccupation with achieving adequate pain relief can be appropriate behavior in a patient with inadequate pain control.
APADAZ, like other opioids, can be diverted for nonmedical use into illicit channels of distribution. Careful record-keeping of prescribing information, including quantity, frequency, and renewal requests, as required by state and federal law, is strongly advised.
Proper assessment of the patient, proper prescribing practices, periodic reevaluation of therapy, and proper dispensing and storage are appropriate measures that help to limit abuse of opioid drugs.

Risks Specific to Abuse of APADAZ
Abuse of APADAZ poses a risk of overdose and death. The risk is increased with concurrent use of APADAZ with alcohol and/or other CNS depressants.

APADAZ is approved for oral use only.

With intravenous abuse, the inactive ingredients in APADAZ can result in local tissue necrosis, infection, pulmonary granulomas, embolism and death, and increased risk of endocarditis and valvular heart injury.

Parenteral drug abuse is commonly associated with transmission of infectious diseases, such as hepatitis and HIV.

Abuse Deterrent Studies
In vitro and human abuse potential studies comparing APADAZ to an immediate-release hydrocodone/acetaminophen tablet control were conducted to assess the potential abuse deterrent properties of APADAZ.

In Vitro Testing

In vitro physical and chemical manipulation studies were performed to evaluate the ability of different methods to extract and convert benzhydrocodone to hydrocodone for the purpose of preparing APADAZ for abuse by the intravenous route or by smoking. The efficiency of extracting benzhydrocodone from APADAZ was similar compared to the efficiency of extracting hydrocodone from the non-abuse-deterrent hydrocodone/acetaminophen control. Further conversion (hydrolysis) of benzhydrocodone to hydrocodone in vitro is a difficult process. Overall, these studies showed no advantage for APADAZ over the hydrocodone/acetaminophen control.

Oral Clinical Abuse Potential Study

In an oral, single-center, randomized, double-blind, active- and placebo-controlled, 7-period, crossover, human abuse potential study, 71 recreational opioid users were randomized into the Treatment Phase; 62 subjects completed the study. Treatment arms included APADAZ (4, 8, and 12 tablets, each containing 6.12 mg benzhydrocodone and 325 mg acetaminophen), hydrocodone/acetaminophen (4, 8 and 12 tablets, each containing 4.54 mg hydrocodone and 325 mg acetaminophen), and placebo. The respective dosage strengths for APADAZ and hydrocodone/acetaminophen contained equimolar amounts of hydrocodone. The rate (Cmax) and extent (AUClast, AUCinf) of hydrocodone exposure following APADAZ administration was comparable to that for hydrocodone/acetaminophen across all 3 dosage strengths. There were no statistically significant differences nor any clinically meaningful differences between APADAZ and the hydrocodone/acetaminophen control for the pre-specified primary endpoint of maximal score (Emax) for Drug Liking VAS or secondary endpoints of Emax for High VAS and Take Drug Again VAS. The results do not support a finding that APADAZ can be expected to deter abuse by the oral route of administration.

Intranasal Clinical Abuse Potential Study

In an intranasal single-center, randomized, double-blind, double-dummy, two-part human abuse potential study, 46 recreational opioid users were randomized into the Treatment Phase; 42 subjects completed the study. Five treatment arms included intranasal crushed and oral APADAZ (2 tablets, each containing 6.12 mg benzhydrocodone and 325 mg acetaminophen), intranasal crushed and oral hydrocodone/acetaminophen (2 tablets, each containing 4.54 mg hydrocodone and 325 mg acetaminophen), and intranasal placebo powder. The respective dosage strengths
for APADAZ and hydrocodone/acetaminophen contained equimolar amounts of hydrocodone.

The pharmacokinetic data showed that overall (AUClast, AUCinf, and Cmax) hydrocodone exposure was comparable between intranasal crushed APADAZ and intranasal crushed hydrocodone/acetaminophen. These treatments were also comparable with cumulative hydrocodone exposure at the timepoints of 4, 8, and 24 hours (AUC0-4, AUC0-8, AUC0-24). Over the first 2 hours post-dosing (AUC0-0.5, AUC0-1, and AUC0-2), the cumulative hydrocodone exposure was lower following intranasal APADAZ compared to intranasal hydrocodone/ acetaminophen.

There were numerically small but not statistically significant differences between APADAZ and the hydrocodone/acetaminophen control observed for the pre-specified primary endpoint, maximum effect on Drug Liking VAS (Emax), and the secondary endpoints of Emaxfor High VAS and Take Drug Again VAS.

Table 3: Summary Statistics of Maximum Scores (Emax) on Drug Liking, High and Take Drug Again, Following Intranasal Administration of APADAZ, Hydrocodone/APAP, and Placebo
VAS Scale (100 point) intranasal (n=42) | APADAZ Crushed | Hydrocodone/APAP Crushed | Placebo
Drug Liking* Mean (SE) Median (Range) | 75.9 (2.3) 74.0 (50-100) | 79.0 (2.7) 80.0 (50-100) | 53.0 (1.2) 51.0 (50-85)
High** Mean (SE) Median (Range) | 61.8 (4.6) 68.5 (0-100) | 59.1 (5.1) 67.5 (0-100) | 8.8 (3.8) 0.0 (0-100)
Take Drug Again* Mean (SE) Median (Range) | 69.5 (3.9) 68.0 (0-100) | 74.5 (3.9) 81.5 (0-100) | 48.2 (2.2) 50.0 (0-100)

* Bipolar scale (0=maximum negative response, 50=neutral response, 100=maximum positive response)
** Unipolar scale (0=maximum negative response, 100=maximum positive response)

Additional secondary analyses of Drug Liking based on area under the effect curve analyses (AUE) for the first half hour, hour, and 2 hours post-dosing, demonstrated numerically small differences between intranasal APADAZ and intranasal hydrocodone/acetaminophen. However, there were no differences between these two treatments with respect to the cumulative High experienced over the first 2 hours post-dosing using similar AUE analyses. There are no data to support that small differences in the early Drug Liking experience over the first 2 hours are clinically relevant findings consistent with possible abuse-deterrent effects, particularly in the setting of the Emax analyses for Drug Liking, Take
Drug Again, and High that do not support a deterrent effect. Based on the overall results, APADAZ cannot be expected to deter abuse by the intranasal route of administration.

Summary
The in vitro studies that evaluated physical manipulation and extraction for the purpose of preparing APADAZ for abuse by the intravenous route or by smoking did not find an advantage for APADAZ over the hydrocodone/acetaminophen control.

The results of the oral and intranasal human abuse potential studies do not support a finding that APADAZ can be expected to deter abuse by the oral or nasal routes of administration.

9.3 Dependence

Both tolerance and physical dependence can develop during use of opioid therapy.

Tolerance is a physiological state characterized by a reduced response to a drug after repeated administration (i.e., a higher dose of a drug is required to produce the same effect that was once obtained at a lower dose).

Physical dependence is a state that develops as a result of a physiological adaptation in response to repeated drug use, manifested by withdrawal signs and symptoms after abrupt discontinuation or a significant dose reduction of a drug.

Withdrawal may be precipitated through the administration of drugs with opioid antagonist activity (e.g., naloxone), mixed agonist/antagonist analgesics (e.g., pentazocine, butorphanol, nalbuphine), or partial agonists (e.g., buprenorphine). Physical dependence may not occur to a clinically significant degree until after several days to weeks of continued use.

Do not abruptly discontinue APADAZ in a patient physically dependent on opioids. Rapid tapering of APADAZ in a patient physically dependent on opioids may lead to serious withdrawal symptoms, uncontrolled pain, and suicide. Rapid discontinuation has also been associated with attempts to find other sources of opioid analgesics, which may be confused with drug-seeking for abuse.

When discontinuing APADAZ, gradually taper the dosage using a patient-specific plan that considers the following: the dose of APADAZ the patient has been taking, the duration of treatment, and the physical and psychological attributes of the patient. To improve the likelihood of a successful taper and minimize withdrawal symptoms, it is important that the opioid tapering schedule is agreed upon by the patient. In patients taking opioids for an extended period of time at high doses, ensure that a multimodal approach to pain management, including mental health support (if needed), is in place prior to initiating an opioid analgesic taper [see Dosage and Administration (2.6), Warnings and Precautions (5.16)] .

Infants born to mothers physically dependent on opioids will also be physically dependent and may exhibit respiratory difficulties and withdrawal signs [see Use in Specific Populations (8.1)] .

10 OVERDOSAGE

Clinical Presentation

Hydrocodone

Acute overdose with hydrocodone can be manifested by respiratory depression, somnolence progressing to stupor or coma, skeletal muscle flaccidity, cold and clammy skin, constricted pupils, and, in some cases, pulmonary edema, bradycardia, hypotension, partial or complete airway obstruction, atypical snoring, and death. Marked mydriasis rather than miosis may be seen with hypoxia in overdose situations [see Clinical Pharmacology (12.2)] .

Acetaminophen
In acute acetaminophen overdosage, dose-dependent, potentially fatal hepatic necrosis is the most serious adverse effect. Renal tubular necrosis, hypoglycemic coma, and thrombocytopenia also occur. Plasma acetaminophen levels > 300 mcg/mL at 4 hours after oral ingestion were associated with hepatic damage in 90% of patients; minimal hepatic damage is anticipated if plasma levels at 4 hours are < 150 mcg/mL or < 37.5 mcg/mL at 12 hours after ingestion. Early symptoms following a potentially hepatotoxic overdose may include: nausea, vomiting, diaphoresis, and general malaise. Clinical and laboratory evidence of hepatic toxicity may not be apparent until 48 to 72 hours post-ingestion.

Treatment of Overdose

A single or multiple drug overdose with hydrocodone and acetaminophen is a potentially lethal polydrug overdose, and consultation with a regional poison control center is recommended. Immediate treatment includes support of cardiorespiratory function and measures to reduce drug absorption. Oxygen, intravenous fluids, vasopressors, assisted ventilation, and other supportive measures should be employed as indicated.

Hydrocodone
In case of overdose, priorities are the reestablishment of a patent and protected airway and institution of assisted or controlled ventilation, if needed. Employ other supportive measures (including oxygen and vasopressors) in the management of circulatory shock and pulmonary edema as indicated. Cardiac arrest or arrhythmias will require advanced life-support measures.

Opioid antagonists, such as naloxone, are specific antidotes to respiratory depression resulting from opioid overdose. For clinically significant respiratory or circulatory depression secondary to opioid overdose, administer an opioid antagonist.

Because the duration of opioid reversal is expected to be less than the duration of action of hydrocodone from APADAZ, carefully monitor the patient until spontaneous respiration is reliably re-established. If the response to an opioid antagonist is suboptimal or only brief in nature, administer additional antagonist as directed by the product’s prescribing information.

In an individual physically dependent on opioids, administration of the recommended usual dosage of the antagonist will precipitate an acute withdrawal syndrome. The severity of the withdrawal symptoms experienced will depend on the degree of physical dependence and the dose of the antagonist administered. If a decision is made to treat serious respiratory depression in the physically dependent patient, administration of the antagonist should be begun with care and by titration with smaller than usual doses of the antagonist.

Acetaminophen

If an acetaminophen overdose is suspected, obtain a serum acetaminophen assay as soon as possible, but no sooner than 4 hours following oral ingestion. Obtain liver function studies initially and repeat at 24-hour intervals. Administer the antidote N-acetylcysteine (NAC) as early as possible. As a guide to treatment of acute ingestion, the acetaminophen level can be plotted against time since oral ingestion on a nomogram (Rumack-Matthew). The lower toxic line on the nomogram is equivalent to 150 mcg/mL at 4 hours and 37.5 mcg/mL at 12 hours. If serum level is above the lower line, administer the entire course of NAC treatment. Withhold NAC therapy if the acetaminophen level is below the lower line.

Gastric decontamination with activated charcoal should be administered just prior to N-acetylcysteine (NAC) to decrease systemic absorption if acetaminophen ingestion is known or suspected to have occurred within a few hours of presentation. Serum acetaminophen levels should be obtained immediately if the patient presents 4 hours or more after ingestion to assess potential risk of hepatotoxicity; acetaminophen levels drawn less than 4 hours post-ingestion may be misleading. To obtain the best possible outcome, NAC should be administered as soon as possible where impending or evolving liver injury is suspected. Intravenous NAC may be administered when circumstances preclude oral administration.

Vigorous supportive therapy is required in severe intoxication. Procedures to limit the continuing absorption of the drug must be readily performed since the hepatic injury is dose-dependent and occurs early in the course of intoxication.

11 DESCRIPTION

APADAZ (benzhydrocodone and acetaminophen) tablet is an immediate-release, fixed-dose combination of an opioid agonist and acetaminophen. APADAZ tablets are white to off-white, capsule shaped tablets that contain 4.08 mg, 6.12 mg, or 8.16 mg of benzhydrocodone (equivalent to 4.45 mg, 6.67 mg, 8.90 mg benzhydrocodone hydrochloride, respectively) and 325 mg of acetaminophen for oral administration.

Benzhydrocodone hydrochloride is a prodrug of hydrocodone. It occurs as a fine white powder and is not affected by light. The chemical name is 6,7-didehydro-4,5α-epoxy-3-methoxy-17- methylmorphinan-6-yl benzoate hydrochloride. The molecular formula is C25H26ClNO4, which corresponds to a molecular weight of 439.93 g/mol. It has the following chemical structure:

Acetaminophen, 4’-hydroxyacetanilide, a slightly bitter, white, odorless, crystalline powder, is a non-opiate, non-salicylate analgesic and antipyretic. The molecular formula for acetaminophen is C8H9NO2, which corresponds to a molecular weight of 151.16 g/mol. It has the following structural formula:

APADAZ tablets contain 4.08 mg, 6.12 mg, or 8.16 mg of benzhydrocodone (equivalent to 4.45 mg, 6.67 mg, 8.90 mg benzhydrocodone hydrochloride, respectively) and 325 mg of acetaminophen and are white to off-white in color. In addition, each tablet contains the following inactive ingredients: crospovidone, microcrystalline cellulose, pregelatinized starch, Povidone K30, and stearic acid.

12 CLINICAL PHARMACOLOGY

12.1 Mechanism of Action

Benzhydrocodone
Benzhydrocodone is a prodrug of hydrocodone.

Hydrocodone
Hydrocodone is a full opioid agonist with relative selectivity for the mu-opioid receptor, although it can interact with other opioid receptors at higher doses. The principal therapeutic action of hydrocodone is analgesia. Like all full opioid agonists, there is no ceiling effect for analgesia with hydrocodone. Clinically, dosage is titrated to provide adequate analgesia and may be limited by adverse reactions, including respiratory and CNS depression.

The precise mechanism of the analgesic action is unknown. However, specific CNS opioid receptors for endogenous compounds with opioid-like activity have been identified throughout the brain and spinal cord and are thought to play a role in the analgesic effects of this drug.

Acetaminophen
Acetaminophen is a non-opioid, non-salicylate analgesic. The site and mechanism for the analgesic effect of acetaminophen has not been determined but is thought to primarily involve central actions.

12.2 Pharmacodynamics

Hydrocodone
Effects on the Central Nervous System
Hydrocodone produces respiratory depression by direct action on brain stem respiratory centers. The respiratory depression involves a reduction in the responsiveness of the brain stem respiratory centers to both increases in carbon dioxide tension and electrical stimulation.

Hydrocodone causes miosis, even in total darkness. Pinpoint pupils are a sign of opioid overdose but are not pathognomonic (e.g., pontine lesions of hemorrhagic or ischemic origins may produce similar findings). Marked mydriasis rather than miosis may be seen with hypoxia in overdose situations.

Effects on the Gastrointestinal Tract and Other Smooth Muscle
Hydrocodone causes a reduction in motility associated with an increase in smooth muscle tone in the antrum of the stomach and duodenum. Digestion of food in the small intestine is delayed and propulsive contractions are decreased. Propulsive peristaltic waves in the colon are decreased, while tone may be increased to the point of spasm, resulting in constipation. Other opioid-induced effects may include a reduction in biliary and pancreatic secretions, spasm of sphincter of Oddi, and transient elevations in serum amylase.

Effects on the Cardiovascular System
Hydrocodone produces peripheral vasodilation which may result in orthostatic hypotension or syncope. Manifestations of histamine release and/or peripheral vasodilation may include pruritus, flushing, red eyes, sweating, and/or orthostatic hypotension.

Caution must be used in hypovolemic patients, such as those suffering acute myocardial infarction, because hydrocodone may cause or further aggravate their hypotension. Caution must also be used in patients with cor pulmonale who have received therapeutic doses of opioids.

Effects on the Endocrine System
Opioids inhibit the secretion of adrenocorticotropic hormone (ACTH), cortisol, and luteinizing hormone (LH) in humans [see Adverse Reactions (6.2)] . They also stimulate prolactin, growth hormone (GH) secretion, and pancreatic secretion of insulin and glucagon.

Use of opioids for an extended period of time may influence the hypothalamic-pituitary-gonadal axis, leading to androgen deficiency that may manifest as low libido, impotence, erectile dysfunction, amenorrhea, or infertility. The causal role of opioids in the clinical syndrome of hypogonadism is unknown because the various medical, physical, lifestyle, and psychological stressors that may influence gonadal hormone levels have not been adequately controlled for in studies conducted to date. Patients presenting with symptoms of androgen deficiency should undergo laboratory evaluation [see Adverse Reactions (6.2)] .

Effects on the Immune System
Opioids have been shown to have a variety of effects on components of the immune system in in vitro and animal models. The clinical significance of these findings is unknown. Overall, the effects of opioids appear to be modestly immunosuppressive.

Concentration–Efficacy Relationships
The minimum effective analgesic concentration will vary widely among patients, especially among patients who have been previously treated with opioid agonists. The minimum effective analgesic concentration of hydrocodone for any individual patient may increase over time due to an increase in pain, the development of a new pain syndrome, and/or the development of analgesic tolerance [see Dosage and Administration (2.1, 2.5)] .

Concentration–Adverse Reaction Relationships
There is a relationship between increasing hydrocodone plasma concentration and increasing frequency of dose-related opioid adverse reactions such as nausea, vomiting, CNS effects, and respiratory depression. In opioid-tolerant patients, the situation may be altered by the development of tolerance to opioid-related adverse reactions [see Dosage and Administration (2.1, 2.3, 2.5)] .

12.3 Pharmacokinetics

APADAZ has met the bioequivalence criteria for hydrocodone AUC and Cmaxto other immediate-release hydrocodone combination products. Benzhydrocodone was not detectable in plasma after oral administration in clinical studies, indicating that exposure to benzhydrocodone was minimal and transient. Steady state with APADAZ is attained within 24 to 36 hours of dosing. The systemic exposure to hydrocodone from APADAZ increases linearly after administration of single and multiple doses of 2 tablets of APADAZ.

Absorption
Single-Dose Studies
In 2 comparative bioavailability studies following oral administration of single dose to healthy subjects under fasted conditions, 6.12 mg/325 mg APADAZ tablet met the bioequivalence criteria for hydrocodone AUC and Cmaxto immediate-release tablet of 7.5 mg hydrocodone/200 mg ibuprofen (N = 28); and the bioequivalence criteria for acetaminophen AUC and Cmaxto immediate-release tablet of 37.5 mg tramadol/325 mg acetaminophen (N = 27).

In a comparative bioavailability study following oral administration of single dose under fasted conditions in 24 healthy subjects comparing 6.12 mg/325 mg APADAZ to immediate-release tablet of 7.5 mg hydrocodone/325 mg acetaminophen, APADAZ met the bioequivalence criteria for hydrocodone Cmaxand AUC; and met the bioequivalence criteria for acetaminophen AUC, with comparable acetaminophen Cmax.

In a study to assess the effect of food on the bioavailability and pharmacokinetics of APADAZ in 38 healthy subjects compared to fasted conditions, co-administration of APADAZ with a high-fat, high-calorie meal showed a slight decrease in the rate but no change in the extent of hydrocodone absorption; and no difference in rate and extent of acetaminophen absorption. The effect of a high-fat, high-calorie meal on pharmacokinetics is similar between APADAZ and immediate-release tablet of 7.5 mg hydrocodone/325 mg acetaminophen. APADAZ can be administered without regard to food. The PK parameters for hydrocodone and acetaminophen after oral administration of APADAZ tablet,
6.12 mg /325 mg under fasted and fed conditions are shown in Table 4 below.

Table 4. PK parameters of hydrocodone and acetaminophen after oral administration of APADAZ tablet, 6.12 mg /325 mg under fasted and fed conditions.
Parameter* | Fed | Fasted
Hydrocodone | Fed | Fasted
Cmax(ng/mL) | 16.04 ± 3.60 (40) | 19.18 ± 4.84 (38)
Tmax(h) | 2.50 (40) [0.50–4.00] | 1.25 (38) [0.50–3.00]
AUCinf(h•ng/mL) | 130.91 ± 29.45 (40) | 125.73 ± 36.78 (38)
t½(h) | 4.53 ± 0.70 (40) | 4.33 ± 0.67 (38)
Acetaminophen
Cmax(μg/mL) | 3.34 ± 1.01 (39) | 4.05 ± 1.30 (38)
Tmax(h) | 1.50 (39) [0.50–4.00] | 1.00 (38) [0.50–3.00]
AUCinf(h•μg/mL) | 15.0 ± 3.53 (36) | 14.7 ± 3.87 (36)
t½(h) | 5.64 ± 1.58 (36) | 4.78 ± 1.30 (36)

* Arithmetic mean ± standard deviation (N) except Tmaxfor which the median (N) [Range] is reported

Multiple-Dose Study
A multiple-dose study in 24 healthy subjects showed no measurable exposure to benzhydrocodone, when 2 tablets of APADAZ, 6.12 /325 mg, was administered orally every 4 hours for a total of 13 doses. Steady state for hydrocodone and acetaminophen was achieved after 24 hours and between 24 and 36 hours, respectively. The accumulation ratios for hydrocodone Cmaxand AUC values were 1.85-fold and 2.03-fold, respectively. The accumulation ratios for acetaminophen Cmaxand AUC values were 1.38-fold and 1.80-fold, respectively.

Elimination
Hydrocodone is eliminated primarily from the kidneys. Elimination of acetaminophen is principally by liver metabolism and subsequent renal excretion of metabolites.

Metabolism
Benzhydrocodone is a prodrug of hydrocodone and is converted to active hydrocodone by enzymes in the intestinal tract.

Hydrocodone exhibits a complex pattern of metabolism, including O-demethylation, N-demethylation, and 6-keto reduction to the corresponding 6-α-and 6-β-hydroxy metabolites. Hydromorphone, a potent opioid, is formed from the O-demethylation of hydrocodone and contributes to the total analgesic effect of hydrocodone. The O- and N- demethylation processes are mediated by separate P-450 isoenzymes: CYP2D6 and CYP3A4, respectively [see Drug Interactions (7)] .

Acetaminophen is primarily metabolized in the liver by first-order kinetics and involves three principal separate pathways:
a) conjugation with glucuronide;
b) conjugation with sulfate; and
c) oxidation via the cytochrome, P450-dependent, mixed-function oxidase enzyme pathway to form a reactive intermediate metabolite, which conjugates with glutathione and is then further metabolized to form cysteine and mercapturic acid conjugates. The principal cytochrome P450 isoenzyme involved appears to be CYP2E1, with CYP1A2 and CYP3A4 as additional pathways.

In adults, the majority of acetaminophen is conjugated with glucuronic acid and, to a lesser extent, with sulfate. These glucuronide-, sulfate-, and glutathione-derived metabolites lack biologic activity. In premature infants, newborns, and young infants, the sulfate conjugate predominates.

Excretion
Hydrocodone and its metabolites are eliminated primarily in the kidneys, with a mean plasma half-life of 4.5 hours.

The half-life of acetaminophen is about 2 to 3 hours in adults. It is somewhat shorter in children and somewhat longer in neonates and in cirrhotic patients. Acetaminophen is eliminated from the body primarily by formation of glucuronide and sulfate conjugates in a dose-dependent manner. Less than 9% of acetaminophen is excreted unchanged in the urine.

Specific Populations
Age
For hydrocodone, no significant pharmacokinetic differences based on age have been demonstrated. For APAP, a population pharmacokinetic analysis of data obtained from a clinical trial in patients with chronic pain treated with immediate-release tablets of 7.5 mg hydrocodone/325 mg acetaminophen, which included 55 patients between 65 and 75 years of age and 19 patients over 75 years of age, showed no significant changes in the pharmacokinetics of acetaminophen in elderly patients with normal renal and hepatic function [see Use in Specific Populations (8.5)] .

Sex
For hydrocodone, no significant pharmacokinetic differences based on gender have been demonstrated.

Renal Impairment
The effect of renal insufficiency on the pharmacokinetics of APADAZ has not been determined [see Use in Specific Populations (8.7)] .

Hepatic Impairment
Because acetaminophen is extensively metabolized by the liver, the use of APADAZ in patients with severe hepatic impairment or severe active liver disease is contraindicated. The pharmacokinetics and tolerability of APADAZ in patients with impaired hepatic function have not been studied [see Contraindications (4), Use in Specific Populations (8.6)] .

13 NONCLINICAL TOXICOLOGY

13.1 Carcinogenesis, Mutagenesis, Impairment of Fertility

Carcinogenesis
Long-term studies to evaluate the carcinogenic potential of benzhydrocodone or the combination of benzhydrocodone and acetaminophen have not been conducted.

Long-term studies in mice and rats have been completed by the National Toxicology Program to evaluate the carcinogenic potential of acetaminophen. In 2-year feeding studies, F344/N rats and B6C3F1 mice were fed a diet containing acetaminophen up to 6000 ppm. Female rats demonstrated equivocal evidence of carcinogenic activity based on increased incidences of mononuclear cell leukemia at 0.8 times the maximum human daily dose (MHDD) of 3.9 grams/day, based on a body surface area comparison. In contrast, there was no evidence of carcinogenic activity in male rats (0.7 times) or mice (1.3-1.5 times the MHDD, based on a body surface area comparison).

Mutagenesis
Benzhydrocodone was positive in an in vitro mammalian cell chromosome aberration assay in the presence of a metabolic activation (S9 mix) and negative in the absence of metabolic activation. Benzhydrocodone was negative in an in vitro bacterial mutation assay as well as in the in vivo rat micronucleus and comet assays.

Acetaminophen was not mutagenic in the bacterial reverse mutation assay (Ames test). In contrast, acetaminophen tested positive in the in vitro mouse lymphoma assay and the in vitro chromosomal aberration assay using human lymphocytes. In the published literature, acetaminophen has been reported to be clastogenic when administered at 1500 mg/kg/day to the rat model (3.7-times the MHDD, based on a body surface area comparison). In contrast, no clastogenicity was noted at a dose of 750 mg/kg/day (1.9-times the MHDD, based on a body surface area comparison), suggesting a threshold effect.

Impairment of Fertility
No nonclinical fertility studies have been conducted with benzhydrocodone or the combination of benzhydrocodone and acetaminophen.

In studies conducted by the National Toxicology Program, fertility assessments with acetaminophen have been completed in Swiss CD-1 mice via a continuous breeding study. There were no effects on fertility parameters in mice consuming up to 1.8 times the MHDD of acetaminophen, based on a body surface area comparison. Although there was no effect on sperm motility or sperm density in the epididymis, there was a significant increase in the percentage of abnormal sperm in mice consuming 1.8 times the MHDD (based on a body surface comparison) and there was a reduction in the number of mating pairs producing a fifth litter at this dose, suggesting the potential for cumulative toxicity with chronic administration of acetaminophen near the upper limit of daily dosing.

Published studies in rodents report that oral acetaminophen treatment of male animals at doses that are 1.2 times the MHDD and greater (based on a body surface comparison) result in decreased testicular weights, reduced spermatogenesis, reduced fertility, and reduced implantation sites in females given the same doses. These effects appear to increase with the duration of treatment.

In a published mouse study, oral administration of 50 mg/kg acetaminophen to pregnant mice from Gestation Day 7 to delivery (0.06 times the MHDD) reduced the number of primordial follicles in female offspring and reduced the percentage of full-term pregnancies and number of pups born to these females exposed to acetaminophen in utero.

In a published study, pregnant rats oral administration of 350 mg/kg acetaminophen (0.9 times the MHDD) from Gestation Day 13 to 21 (dams), reduced the number of germ cells in the fetal ovary and decreased ovary weight and reduced number of pups per litter in F1 females as well as reduced ovary weights in F2 females.

16 HOW SUPPLIED/STORAGE AND HANDLING

APADAZ (benzhydrocodone and acetaminophen) tablets are available as follows:

Capsule-shaped, white tablets debossed with “KP201” on one side and “445” on the opposite side, containing 4.08 mg benzhydrocodone (equivalent to 4.45 mg benzhydrocodone hydrochloride) and 325 mg acetaminophen supplied as:

- bottles of 100 (NDC 70040-0145-1)

Capsule-shaped, white tablets debossed with “KP201” on one side and blank on the opposite side, containing 6.12 mg benzhydrocodone (equivalent to 6.67 mg benzhydrocodone hydrochloride) and 325 mg acetaminophen supplied as:

- bottles of 100 (NDC 70040-0167-1)

Capsule-shaped, white tablets debossed with “KP201” on one side and “890” on the opposite side containing 8.16 mg benzhydrocodone (equivalent to 8.90 mg benzhydrocodone hydrochloride) and 325 mg acetaminophen supplied as:

- bottles of 100 (NDC 70040-0189-1)

Flush expired or unused APADAZ tablets that are no longer needed down the toilet or contact the Drug Enforcement Administration (DEA) to find the location of an authorized collector (1-800-882-9539).

Storage
Store at 20°C to 25°C (68°F to 77°F). Excursions permitted between 15°C to 30°C (59°F to 86°F) [See USP Controlled Room Temperature].

Store APADAZ securely and dispose of properly.

17 PATIENT COUNSELING INFORMATION

Advise the patient to read the FDA-approved patient labeling (Medication Guide).

Storage and Disposal:

Because of the risks associated with accidental ingestion, misuse, and abuse, advise patients to store APADAZ securely, out of sight and reach of children, and in a location not accessible by others, including visitors to the home. Inform patients that leaving APADAZ unsecured can pose a deadly risk to others in the home [see Warnings and Precautions (5.1, 5.2), Drug Abuse and Dependence (9.2)] .

Advise patients and caregivers that when medicines are no longer needed, they should be disposed of promptly. Expired, unwanted, or unused APADAZ should be disposed of by flushing the unused medication down the toilet if a drug take-back option is not readily available. Inform patients that they can visit www.fda.gov/drugdisposalfor a complete list of medicines recommended for disposal by flushing, as well as additional information on disposal of unused medicines.

Addiction, Abuse, and Misuse

Inform patients that the use of APADAZ, even when taken as recommended, can result in addiction, abuse, and misuse, which can lead to overdose and death [see Warnings and Precautions (5.1)] . Instruct patients not to share APADAZ with others and to take steps to protect APADAZ from theft or misuse.

Life-Threatening Respiratory Depression

Inform patients of the risk of life-threatening respiratory depression, including information that the risk is greatest when starting APADAZ or when the dosage is increased, and that it can occur even at recommended dosages.

Educate patients and caregivers on how to recognize respiratory depression and emphasize the importance of calling 911 or getting emergency medical help right away in the event of a known or suspected overdose [see Warnings and Precautions (5.3)] .

Accidental Ingestion

Inform patients that accidental ingestion, especially by children, may result in respiratory depression or death [see Warnings and Precautions (5.3)] .

Interactions with Benzodiazepines and Other CNS Depressants

Inform patients that potentially fatal additive effects may occur if APADAZ is used with benzodiazepines or other CNS depressants, including alcohol, and not to use these unless supervised by a healthcare provider [see Warnings and Precautions (5.7) , Drug Interactions (7)].

Patient Access to Naloxone for the Emergency Treatment of Opioid Overdose

Discuss with the patient and caregiver the availability of naloxone for the emergency treatment of opioid overdose, both when initiating and renewing treatment with APADAZ. Inform patients and caregivers about the various ways to obtain naloxone as permitted by individual state naloxone dispensing and prescribing requirements or guidelines (e.g., by prescription, directly from a pharmacist, or as part of a community-based program) [see Dosage and Administration (2.2), Warnings and Precautions (5.2)] .

Educate patients and caregivers on how to recognize the signs and symptoms of an overdose.

Explain to patients and caregivers that naloxone’s effects are temporary, and that they must call 911 or get emergency medical help right away in all cases of known or suspected opioid overdose, even if naloxone is administered [see Overdosage (10)] .

If naloxone is prescribed, also advise patients and caregivers:

- How to treat with naloxone in the event of an opioid overdose
- To tell family and friends about their naloxone and to keep it in a place where family and friends can access it in an emergency
- To read the Patient Information (or other educational material) that will come with their naloxone. Emphasize the importance of doing this before an opioid emergency happens, so the patient and caregiver will know what to do.

Maximum Daily Acetaminophen Use

Advise patients not to take more than 4,000 milligrams of acetaminophen per day and call their healthcare provider if they have taken more than the recommended dose. Advise patients not to take APADAZ in combination with other tramadol or acetaminophen-containing products, including over-the-counter preparations [(see Warnings and Precautions (5.6)].

Hyperalgesia and Allodynia

Inform patients and caregivers not to increase opioid dosage without first consulting a clinician. Advise patients to seek medical attention if they experience symptoms of hyperalgesia, including worsening pain, increased sensitivity to pain, or new pain [see Warnings and Precautions (5.8), Adverse Reactions (6.2)].

Serotonin Syndrome

Inform patients that opioids could cause a rare but potentially life-threatening condition called serotonin syndrome resulting from concomitant administration of serotonergic drugs. Warn patients of the symptoms of serotonin syndrome and to seek medical attention right away if symptoms develop. Instruct patients to inform their healthcare providers if they are taking, or plan to take serotonergic medications [see Drug Interactions (7)].

MAOI Interaction

Inform patients to avoid taking APADAZ while using any drugs that inhibit monoamine oxidase. Patients should not start MAOIs while taking APADAZ [see Drug Interactions (7)].

Important Administration Instructions

Instruct patients how to properly take APADAZ [see Dosage and Administration (2), Warnings and Precautions (5)] .

- Do not take more than 4,000 milligrams of acetaminophen per day. Call your healthcare provider if you took more than the recommended dose.
- Use APADAZ exactly as prescribed to reduce the risk of life-threatening adverse reactions (e.g., respiratory depression).

Important Discontinuation Instructions

In order to avoid developing withdrawal symptoms, instruct patients not to discontinue APADAZ without first discussing a tapering plan with the prescriber [see Dosage and Administration (2.6)] .

Driving or Operating Heavy Machinery

Inform patients that APADAZ may impair the ability to perform potentially hazardous activities such as driving a car or operating heavy machinery. Advise patients not to perform such tasks until they know how they will react to the medication [see Warnings and Precautions (5.17)].

Constipation

Advise patients of the potential for severe constipation, including management instructions and when to seek medical attention [see Adverse Reactions (6)].

Adrenal Insufficiency

Inform patients that opioids could cause adrenal insufficiency, a potentially life-threatening condition. Adrenal insufficiency may present with non-specific symptoms and signs such as nausea, vomiting, anorexia, fatigue, weakness, dizziness, and low blood pressure. Advise patients to seek medical attention if they experience a constellation of these symptoms [see Warnings and Precautions (5.9)].

Hypotension

Inform patients that APADAZ may cause orthostatic hypotension and syncope. Instruct patients how to recognize symptoms of low blood pressure and how to reduce the risk of serious consequences should hypotension occur (e.g., sit or lie down, carefully rise from a sitting or lying position) [see Warnings and Precautions (5.10)].

Anaphylaxis

Inform patients that anaphylaxis have been reported with ingredients contained in APADAZ. Advise patients how to recognize such a reaction and when to seek medical attention [see Contraindications (4), Warnings and Precautions (5.13), Adverse Reactions (6)].

Pregnancy

Neonatal Opioid Withdrawal Syndrome

Inform female patients of reproductive potential that use of APADAZ for an extended period of time during pregnancy can result in neonatal opioid withdrawal syndrome, which may be life-threatening if not recognized and treated [see Warnings and Precautions (5.4), Use in Specific Populations (8.1)].

Embryo-Fetal Toxicity

Inform female patients of reproductive potential that APADAZ can cause fetal harm and to inform their healthcare provider of a known or suspected pregnancy [see Use in Specific Populations (8.1)].

Lactation

Advise nursing mothers to carefully observe infants for increased sleepiness (more than usual), breathing difficulties, or limpness. Instruct nursing mothers to seek immediate medical care if they notice these signs [see Use in Specific Populations (8.2)].

Infertility

Inform patients that use of opioids for an extended period of time may cause reduced fertility. It is not known whether these effects on fertility are reversible [see Use in Specific Populations (8.3)].

Serious Skin Reactions

Advise patients to stop APADAZ immediately if they develop any type of rash and to contact their healthcare provider as soon as possible [see Warnings and Precautions (5.11) ].

Manufactured for:
Zevra Therapeutics, Inc.
1180 Celebration Blvd., Ste 103
Celebration, FL 34747

Manufacturer’s Code: 70040
Item ID#: 6398/05 Rev. 11/2024

Made in U.S.A

Medication Guide APADAZ® (ap’ ah daz) (benzhydrocodone and acetaminophen) tablet, CII

APADAZ is:

- A strong prescription pain medicine that contains an opioid (narcotic) and the medicine acetaminophen. APADAZ is used to manage short-term pain (no more than 14 days), when other pain treatments such as non-opioid pain medicines do not treat your pain well enough or you cannot tolerate them.
- An opioid pain medicine that can put you at risk for overdose and death. Even if you take your dose correctly as prescribed you are at risk for opioid addiction, abuse, and misuse that can lead to death.

Important information about APADAZ:

- Get emergency help or call 911 right away if you take too much APADAZ (overdose).When you first start taking APADAZ, when your dose is changed, or if you take too much (overdose), serious or life-threatening breathing problems that can lead to death may occur. Talk to your healthcare provider about naloxone, a medicine for the emergency treatment of an opioid overdose.
- Never give anyone else your APADAZ. They could die from taking it. Selling or giving away APADAZ is against the law.
- Store APADAZ securely, out of sight and reach of children, and in a location not accessible by others, including visitors to the home.
- Get emergency help right away if you take more than 4,000 mg of acetaminophen in 1 day. Taking APADAZ with other products that contain acetaminophen can lead to serious liver problems and death.

Do not take APADAZ if you have:

- severe asthma, trouble breathing, or other lung problems.
- an allergy to hydrocodone or acetaminophen.
- a bowel blockage or have narrowing of the stomach or intestines.
- severe liver problems.

Before taking APADAZ, tell your healthcare provider if you have a history of:

- head injury, seizures.
- liver, kidney, thyroid problems
- problems urinating
- pancreas or gallbladder problems
- abuse of street or prescription drugs, alcohol addiction, opioid overdose, or mental health problems.

Tell your healthcare provider if you are:

- noticing your pain getting worse.If your pain gets worse after you take APADAZ, do not take more of APADAZ without first talking to your healthcare provider. Talk to your healthcare provider if the pain that you have increases, if you feel more sensitive to pain, or if you have new pain after taking APADAZ.
- pregnant or planning to become pregnant.Use of APADAZ for an extended period of time during pregnancy can cause withdrawal symptoms in your newborn baby that could be life-threatening if not recognized and treated.
- breastfeeding. APADAZ passes into breast milk and may harm your baby. Carefully observe infants for increased sleepiness (more than usual), breathing difficulties, or limpness. Seek immediate medical care if you notice these signs.
- living in a household where there are small children or someone who has abused street or prescription drugs.
- taking prescription or over-the-counter medicines, vitamins, or herbal supplements. Taking APADAZ with certain other medicines can cause serious side effects that could lead to death.

When taking APADAZ:

- Do not change your dose. Take APADAZ exactly as prescribed by your healthcare provider. Use the lowest dose possible for the shortest time needed.
- For acute (short-term) pain, you may only need to take APADAZ for a few days. You may have some APADAZ left over that you did not use. See disposal information at the bottom of this section for directions on how to safely throw away (dispose of) your unused APADAZ.
- Take your prescribed dose every 4 to 6 hours as needed for pain. Do not take more than your prescribed dose. If you miss a dose, take your next dose at your usual time.
- Call your healthcare provider if the dose you are taking does not control your pain.
- If you have been taking APADAZ regularly, do not stop taking APADAZ without talking to your healthcare provider.
- Dispose of expired, unwanted, or unused APADAZ by promptly flushing down the toilet, if a drug take-back option is not readily available. Visit www.fda.gov/drugdisposalfor additional information on disposal of unused medicines.

While taking APADAZ DO NOT:

- Drive or operate heavy machinery, until you know how APADAZ affects you. APADAZ can make you sleepy, dizzy, or lightheaded.
- Drink alcohol or use prescription or over-the-counter medicines that contain alcohol. Using products containing alcohol during treatment with APADAZ may cause you to overdose and die.
- Do not take other products that contain acetaminophen while taking APADAZ.

The possible side effects of APADAZ:

- constipation, nausea, sleepiness, vomiting, tiredness, headache, dizziness, abdominal pain, and skin rash. Call your healthcare provider if you have any of these symptoms and they are severe.

Get emergency medical help or call 911 right away if you have:

- trouble breathing, shortness of breath, fast heartbeat, chest pain, swelling of your face, tongue, or throat, extreme drowsiness, light-headedness when changing positions, feeling faint, agitation, high body temperature, trouble walking, stiff muscles, or mental changes such as confusion.
- rash with hives, sores in your mouth or eyes, or your skin blisters and peels.

These are not all the possible side effects of APADAZ. Call your healthcare provider for medical advice about side effects. You may report side effects to FDA at 1-800-FDA-1088. For more information go to dailymed.nlm.nih.gov

Manufactured for: Zevra Therapeutics, Inc, Celebration, FL 34747, www.zevra.comor call 1-888-958-1253.

This Medication Guide has been approved by the U.S. Food and Drug Administration.Issued: 12/2023